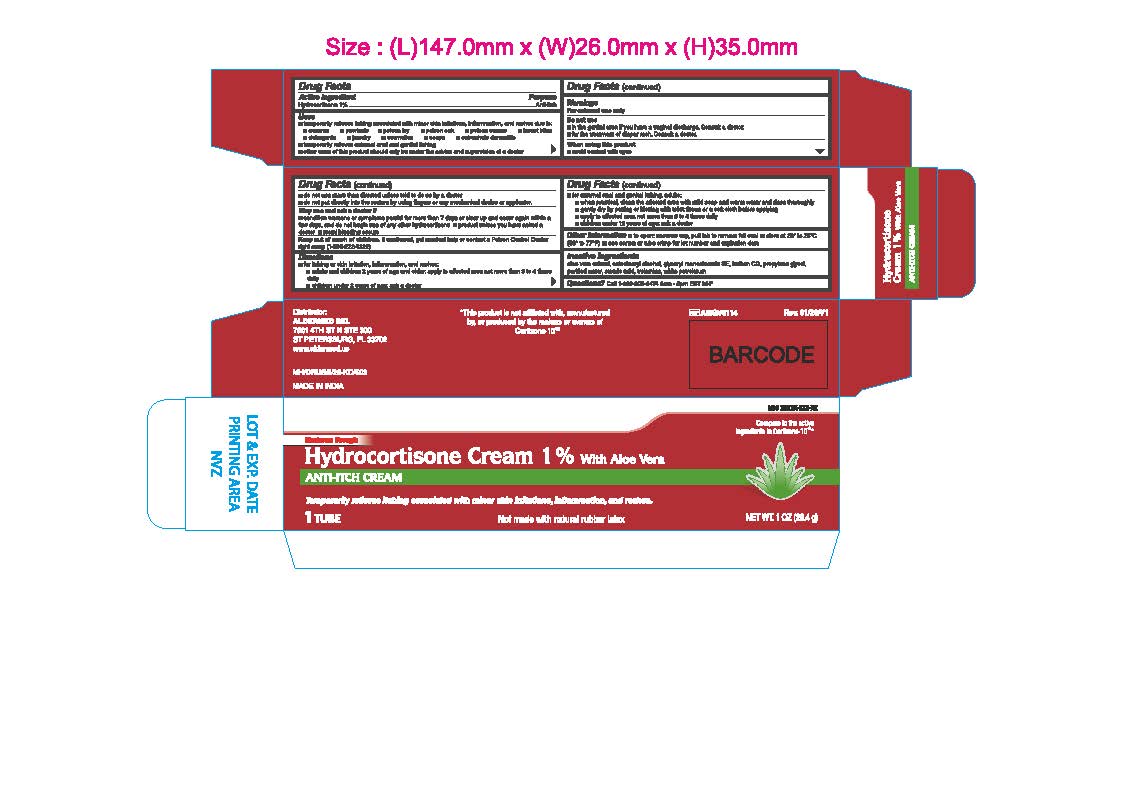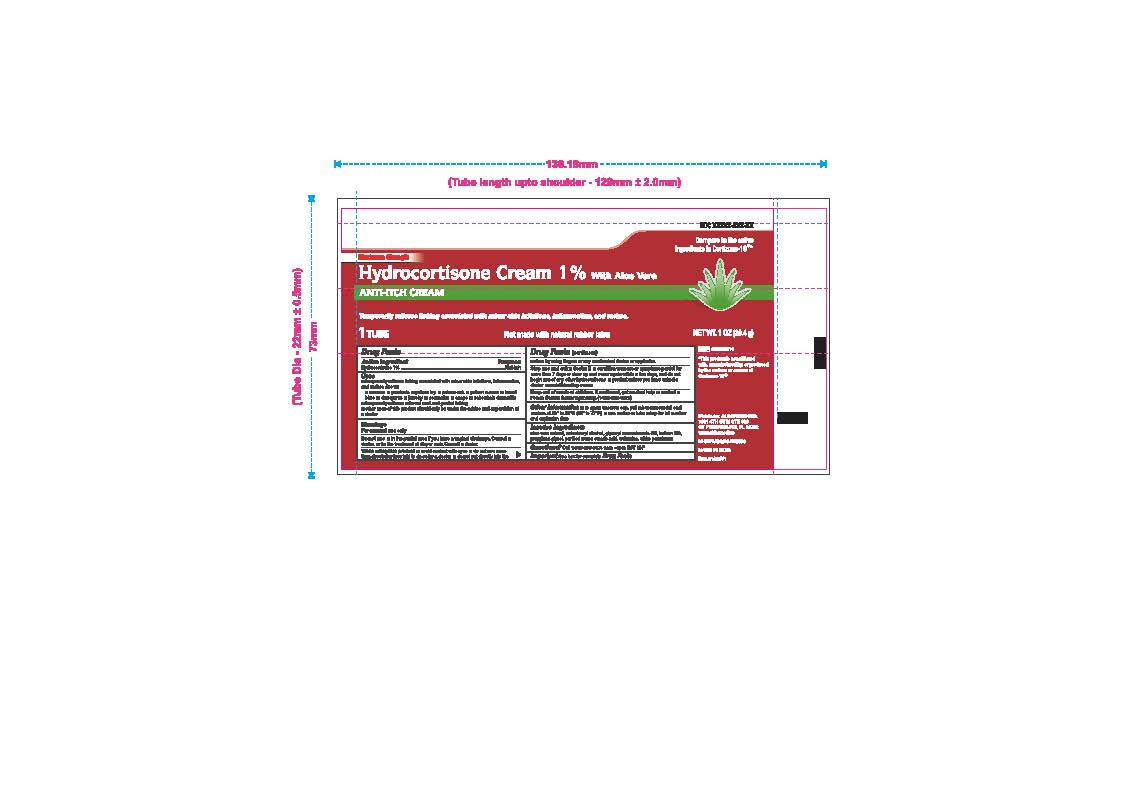 DRUG LABEL: Hydrocortisone
NDC: 87236-003 | Form: CREAM
Manufacturer: Aldermed Inc.
Category: otc | Type: HUMAN OTC DRUG LABEL
Date: 20260210

ACTIVE INGREDIENTS: HYDROCORTISONE 1 g/100 g
INACTIVE INGREDIENTS: PROPYLENE GLYCOL; WHITE PETROLATUM; TROLAMINE; STEARIC ACID; ALOE VERA LEAF; CETOSTEARYL ALCOHOL; METHYLCHLOROISOTHIAZOLINONE/METHYLISOTHIAZOLINONE MIXTURE; GLYCERYL MONOSTEARATE; WATER

Hydrocortisone Cream 1% with Aloe

Drug Facts

Active ingredient

Hydrocortisone 1%

Purpose

Anti-itch

Uses

- temporarily relieves itching associated with minor skin irritations, inflammation, and rashes due to
  - eczema
  - psoriasis
  - poison ivy
  - poison oak
  - poison sumac
  - insect bites
  - detergents
  - jewelry
  - cosmetics
  - soaps
  - seborrheic dermatitis
- temporarily relieves external anal and genital itching
- other uses of this product should be only under the advice and supervision of a doctor

Warnings

For external use only

Do not use

- in the genital area if you have a vaginal discharge. Consult a doctor.
- for the treatment of diaper rash. Consult a doctor.

When using this product

- avoid contact with eyes
- do not use more than directed unless told to do so by a doctor
- do not put directly into the rectum by using fingers or any mechanical device or applicator

Stop use and ask a doctor if

- condition worsens, symptoms persist for more than 7 days or clear up and occur again within a few days, and do not begin use of any other hydrocortisone product unless you have asked a doctor
- rectal bleeding occurs

Keep out of reach of children

If swallowed, get medical help or contact a Poison Control Center right away. (1-800-222-1222)

Directions

- for itching of skin irritation, inflammation, and rashes
- adults and children 2 years of age and older: apply to affected area not more than 3 to 4 times daily
- children under 2 years of age: ask a doctor

- for external anal and genital itching, adults:
- when practical, clean the affected area with mild soap and warm water and rinse thoroughly
- gently dry by patting or blotting with toilet tissue or a soft cloth before applying
- apply to affected area not more than 3 to 4 times daily
- children under 12 years of age: ask a doctor

Other information

- To open, unscrew cap, pull tab to remove foil seal
- store at room temperature 20°-25°C (68-77°F)
- see crimp of tube or carton for lot Number and expiration date

Inactive ingredients

Aloe Vera Extract, Cetostearyl Alcohol, Glyceryl Monostearate SE, Kathon CG, Propylene Glycol, Purified Water, Stearic Acid, Trolamine, White Petrolatum

Questions or Comments?

Call 1-833-605-8474 9am-5pm EST M-F